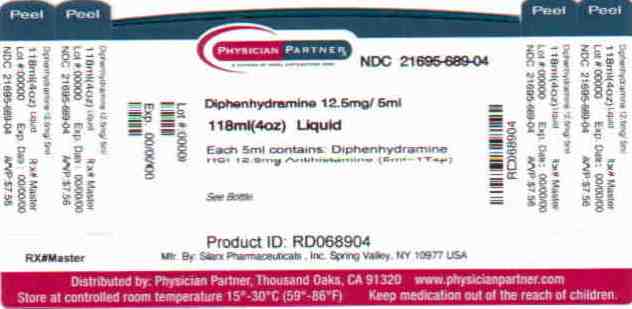 DRUG LABEL: Siladryl Allergy Medicine
NDC: 21695-689 | Form: LIQUID
Manufacturer: Rebel Distributors Corp
Category: otc | Type: HUMAN OTC DRUG LABEL
Date: 20110209

ACTIVE INGREDIENTS: diphenhydramine hydrochloride 12.5 mg/5 mL
INACTIVE INGREDIENTS: anhydrous citric acid; methylparaben; propylene glycol; propylparaben; saccharin sodium; sodium citrate; sorbitol; water; D&C red no. 33; FD&C red no. 40

Siladryl Allergy Liquid Medicine

Active Ingredient: Diphenhydramine HCl 12.5 mg (in each 5 mL*)

* 5 mL = 1 teaspoonful

Purpose: Antihistamine

Uses

- temporarily relieves these symptoms due to hay fever or other upper respiratory allergies:
  - runny nose
  - sneezing
  - itchy, watery eyes
  - itching of the nose or throat
- temporarily relieves these symptoms due to common cold:
  - runny nose
  - sneezing

Warnings

Do not use with any other product containing diphenhydramine, including one applied topically.

Ask a doctor before use if you have

- glaucoma
- trouble urinating due to an enlarged prostate gland
- a breathing problem such as emphysema or chronic bronchitis
- a sodium restricted diet

Ask a doctor or pharmacist before use if you are taking sedatives or tranquilizers

When using this product

- marked drowsiness may occur
- avoid alcoholic drinks
- alcohol, sedatives, and tranquilizers may increase drowsiness
- be careful when driving a motor vehicle or operating machinery
- excitability may occur, especially in children

PREGNANCY OR BREAST FEEDING

If pregnant or breast-feeding, ask a health professional before use.

Keep out of reach of children. In case of overdose, get medical help or contact a Poison Control Center right away.

Directions

- repeat dose every 4 to 6 hours
- do not take more than 6 doses in any 24-hour period

adults and children 12 years and over | 2 to 4 teaspoonfuls
children 6 to under 12 years | 1 to 2 teaspoonfuls
children under 6 years | DO NOT USE

Other information

Store at room temperature 20°-25°C (68°-77°F).

Inactive ingredients

citric acid, D&C red no. 33, FD&C red no. 40, black cherry flavor, methylparaben, propylene glycol, propylparaben, saccharin sodium, sodium citrate, sorbitol, water.

Questions

888-974-5279

† This product is not manufactured or distributed by Warner-Lambert Consumer Healthcare, owner of the registered trademark Benadryl®.

Manufactured by:
Silarx Pharmaceuticals, Inc.
19 West Street
Spring Valley, NY 10977
USA

Repackaged by:

Rebel Distributors Corp

Thousand Oaks, CA 91320